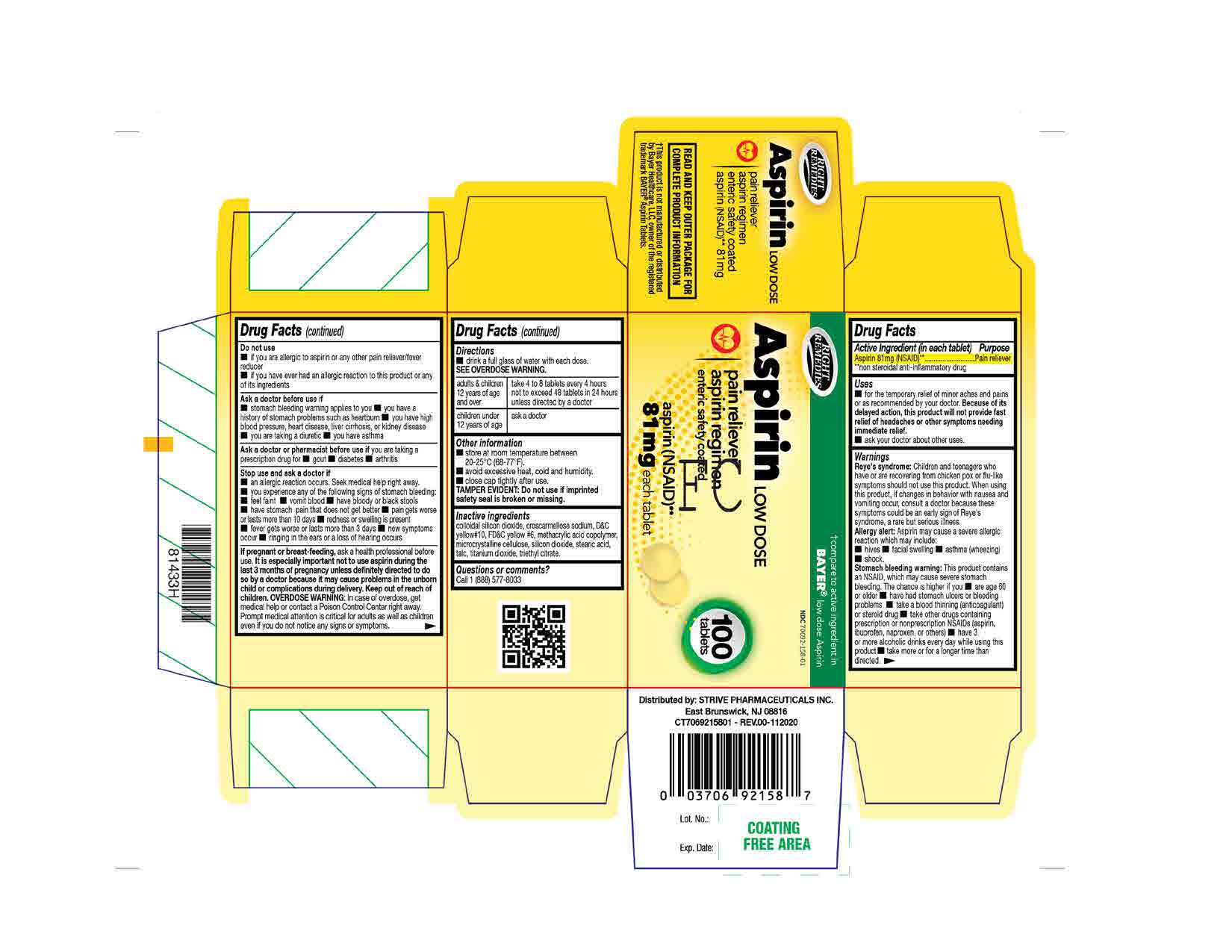 DRUG LABEL: Aspirin 81mg
NDC: 70692-158 | Form: TABLET
Manufacturer: Strive Pharmaceuticals Inc.
Category: otc | Type: HUMAN OTC DRUG LABEL
Date: 20220412

ACTIVE INGREDIENTS: ASPIRIN 81 mg/1 1
INACTIVE INGREDIENTS: TITANIUM DIOXIDE; TRIETHYL CITRATE; SILICON DIOXIDE; FD&C YELLOW NO. 6; D&C YELLOW NO. 10; METHACRYLIC ACID - ETHYL ACRYLATE COPOLYMER (1:1) TYPE A; STEARIC ACID; TALC; CELLULOSE, MICROCRYSTALLINE; CROSCARMELLOSE SODIUM

Right Remedies Aspirin Low Dose
Aspirin 81mg

ACTIVE INGREDIENT

Aspirin 81mg (NSAID)

INACTIVE INGREDIENT

colloidal silicon dioxide, croscarmellose sodium, D&C yellow #10, FD&C yellow #6, methacrylic acid copolymer, microcrytalline cellulose, silicon dioxide, stearic acid, talc, titanium dioxide, triethyl citrate

DOSAGE AND ADMINISTRATION

* drink a full glass of water with each dose SEE OVERDOSE WARNING.

adults and children 12 years of age and over | take 4 to 8 tablets every 4 hours not to exceed 48 tablets in 24 hours unless directed by a doctor
children under 12 years of age | ask a doctor

INDICATIONS AND USAGE

* for the temporary relief of minor aches and pains or as recommended by your doctor. Because of its delayed action, this product will not provide fast relief of headaches or other symptoms needing immediate relief.

*ask your doctor about other uses.

WARNINGS

Reye’s syndrome: Children and teenagers who have or are recovering from chicken pox or flu-like symptoms should not use this product. When using this product, if changes in behavior with nausea and vomiting occur, consult a doctor because these symptoms could be an early sign of Reye’s syndrome, a rare but serious illness.

Allergy alert: Aspirin may cause a severe allergic reaction which may include:

- Hives
- Facial swelling
- Asthma (wheezing)
- Shock

Stomach bleeding warning: This product contains an NSAID, which may cause severe stomach bleeding. The chance is higher if you

- Are age 60 or older
- Have had stomach ulcers or bleeding problems
- Take a blood thinning (anticoagulant)or steroid drug
- Take other drugs containing prescription or nonprescription NSAIDs (aspirin, ibuprofen, naproxen or others)
- Have 3 or more alcoholic drinks everyday while using this product
- Take more or for a longer time than directed.

Do not use

- If you are allergic to aspirin or any other pain reliever/fever reducer.\
- If you have ever had an allergic reaction to this product or any of its ingredients.

Ask a doctor before use if

- Stomach bleeding warning applies to you
- You have a history of stomach problems such as heartburn
- You have high blood pressure, heart disease, liver cirrhosis, or kidney disease
- You are taking a diuretic
- You have asthma

Ask a doctor or pharmacist before use if you are taking a prescription drug for

- Gout
- Diabetes
- Arthritis

Stop use and ask a doctor if

- An allergic reaction occurs. Seek medical help right away.
- You experience any of the following signs of stomach bleeding:
- Feel faint
- Vomit blood
- Have bloody or black stools
- Have stomach pain that does not get better
- Pain gets worse or last more than 10 days
- Redness or swelling is present
- Fever gets worse or last more than 3 days
- New symptoms occur
- Ringing in the ears or loss of hearing occurs

If pregnant or breast-feeding, ask a health professional before use. It is especially important not to use aspirin during the last 3 months of pregnancy unless definitely directed to do so by a doctor because it may cause problems in the unborn child or complications during delivery.

Keep out of reach of children.

OVERDOSE WARNING: In case of overdose, get medical help or contact a Poison Control right away. Prompt medical attention is critical for adults as well as children eve if you do not notice any signs or symptoms.

Keep out of reach of children.

OVERDOSE WARNING: In case of overdose, get medical help or contact a Poison Control right away. Prompt medical attention is critical for adults as well as children eve if you do not notice any signs or symptoms.

PURPOSE

Pain reliever

OTHER SAFETY INFORMATION

* store at room temperature 20 - 25°C (68 - 77°F).

* avoid excessive heat, cold and humidity.

* close cap tightly after use.